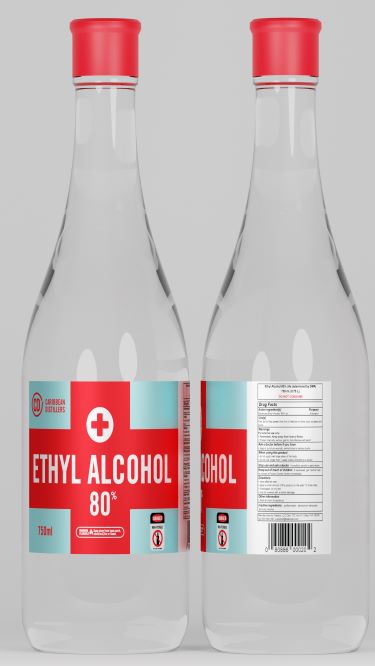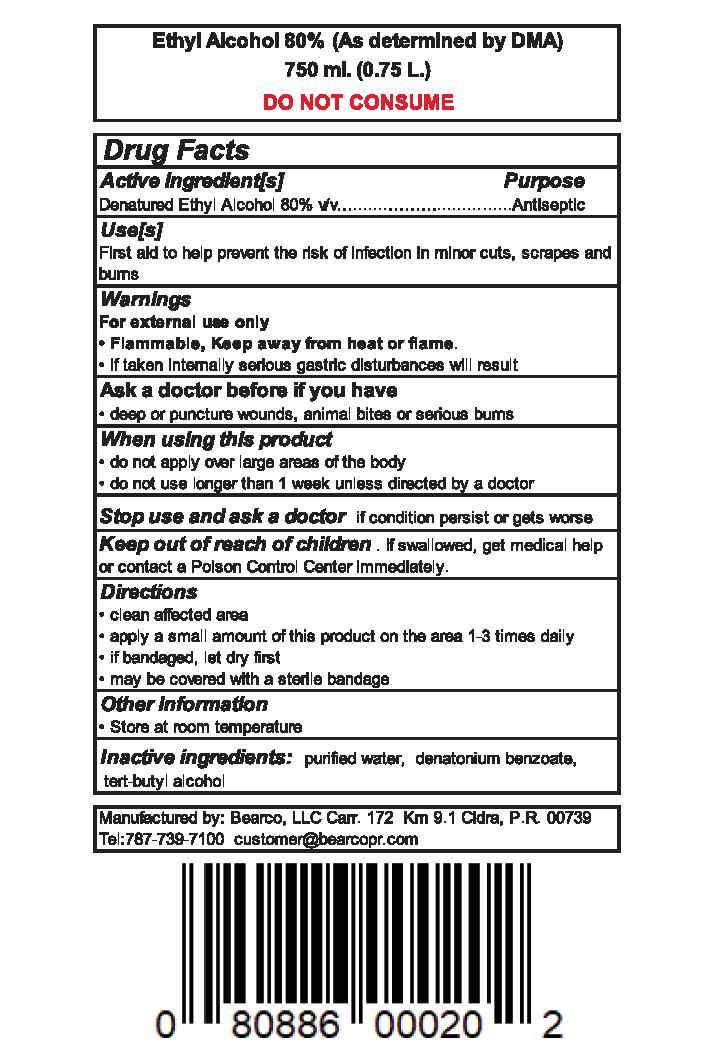 DRUG LABEL: ETHYL ALCOHOL 80 PERCENT
NDC: 74336-800 | Form: LIQUID
Manufacturer: CLUB CARIBE
Category: otc | Type: HUMAN OTC DRUG LABEL
Date: 20200625

ACTIVE INGREDIENTS: ALCOHOL 80 mL/100 mL
INACTIVE INGREDIENTS: WATER; DENATONIUM BENZOATE

ETHYL ALCOHOL 80 PERCENT